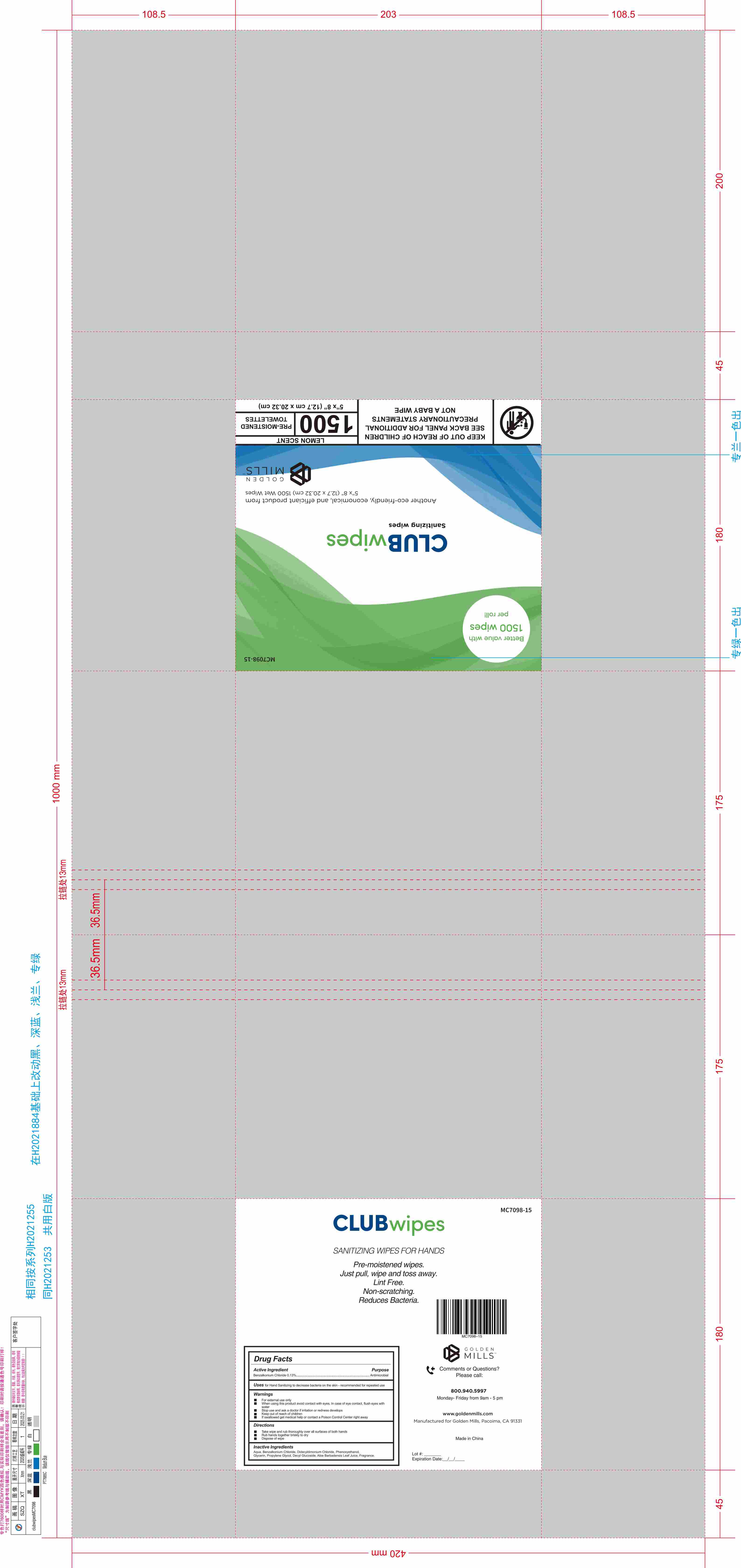 DRUG LABEL: Club Wipes Sanitizing Wipes,Lemon Scent,1500ct
NDC: 85989-002 | Form: PATCH
Manufacturer: Hangzhou Yida Technology Co., Ltd.
Category: otc | Type: HUMAN OTC DRUG LABEL
Date: 20251105

ACTIVE INGREDIENTS: BENZALKONIUM CHLORIDE 1.3 mg/1 g
INACTIVE INGREDIENTS: ALOE VERA LEAF; GLYCERIN; WATER; DECYL GLUCOSIDE

ACTIVE INGREDIENT

Benzalkonium Chloride 0.13%

PURPOSE

for Hand Sanitizing to decrease on the skin - recommended for repeated use

Keep out of reach of children

If swallowed get medical help or contact a Poison Control Center right away

WARNINGS

For external use only

When using this product

avoid contact with eyes. In case of eye contact, flush eyes with water

Stop use and ask a doctor

if irritation or redness develops

INDICATIONS AND USAGE

Rub hands together briskly to dry
Dispose of wipe

DOSAGE AND ADMINISTRATION

Take wipe and rub thoroughly over all surfaces or both hands

INACTIVE INGREDIENT

Purified Water, Glycerin, Aloe Barbadensis Leaf Juice, Decyl Glucoside